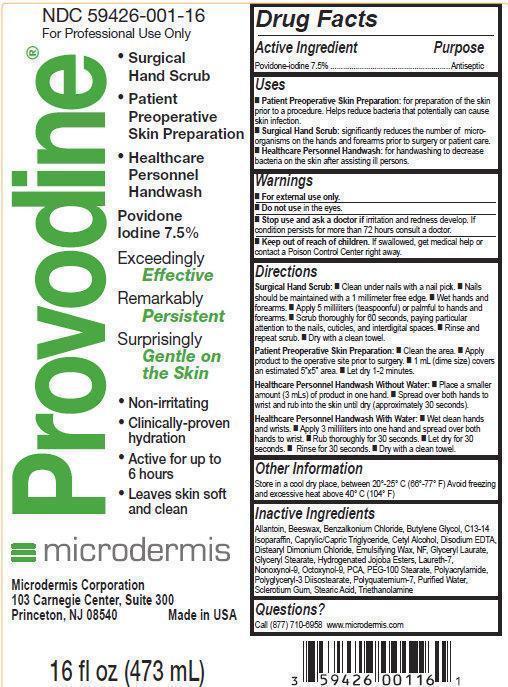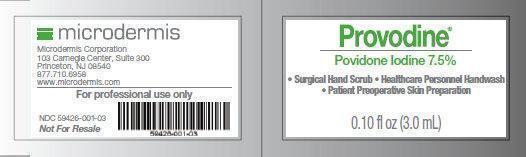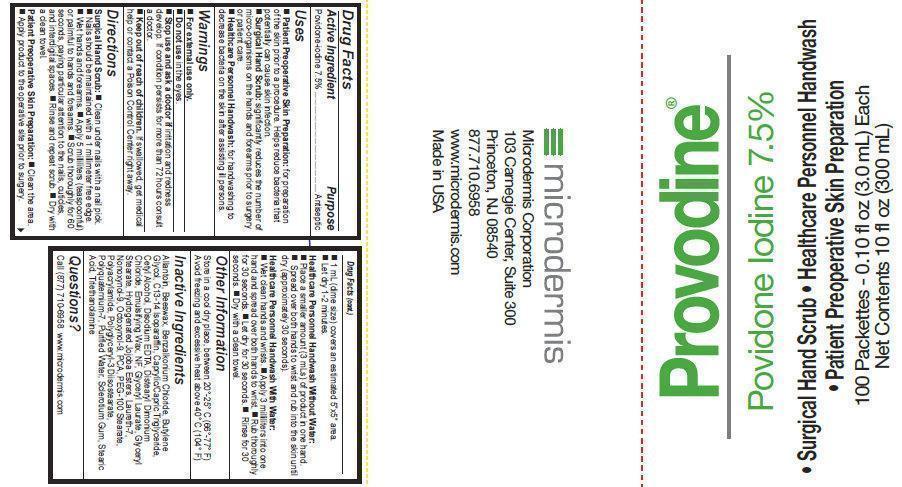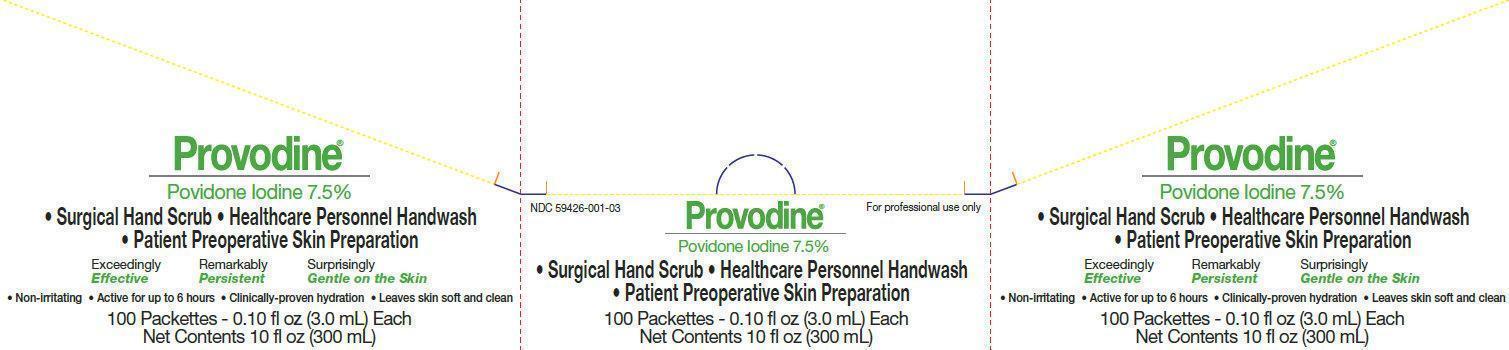 DRUG LABEL: Provodine
NDC: 59426-001 | Form: EMULSION
Manufacturer: Microdermis Corporation
Category: otc | Type: HUMAN OTC DRUG LABEL
Date: 20150702

ACTIVE INGREDIENTS: POVIDONE-IODINE 7.5 mg/1 mL
INACTIVE INGREDIENTS: ALLANTOIN; YELLOW WAX; BENZALKONIUM CHLORIDE; BUTYLENE GLYCOL; C13-14 ISOPARAFFIN; MEDIUM-CHAIN TRIGLYCERIDES; CETYL ALCOHOL; EDETATE DISODIUM; DISTEARYLDIMONIUM CHLORIDE; GLYCERYL LAURATE; GLYCERYL MONOSTEARATE; LAURETH-7; NONOXYNOL-9; OCTOXYNOL-9; PIDOLIC ACID; PEG-100 STEARATE; POLYACRYLAMIDE (10000 MW); POLYGLYCERYL-3 DIISOSTEARATE; POLYQUATERNIUM-7 (70/30 ACRYLAMIDE/DADMAC; 1600 KD); WATER; BETASIZOFIRAN; STEARIC ACID; TROLAMINE

Provodine

Active ingredient

Povidone-iodine 7.5%

Purpose

Antiseptic

Uses

■ Patient Preoperative Skin Preparation: for preparation of the skin prior to a procedure. Helps reduce bacteria that potentially can cause skin infection.

■ Surgical Hand Scrub: significantly reduces the number of micro-organisms on the hands and forearms prior to surgery or patient care.

■ Healthcare Personnel Handwash: for handwashing to decrease bacteria on the skin after assisting ill persons.

Warnings

For external use only

Do not use in the eyes

Stop use and ask a doctor if

irritation and redness develop. If condition persists for more than 72 hours consult a doctor.

Keep out of reach of children.

If swallowed, get medical help or contact a Poison Control Center right away.

Directions

Surgical Hand Scrub:

■ Clean under nails with a nail pick.

■ Nails should be maintained with a 1 millimeter free edge.

■ Wet hands and forearms. ■ Apply 5 milliliters (teaspoonful) or palmful to hands and forearms.

■ Scrub thoroughly for 60 seconds, paying particular attention to the nails, cuticles, and interdigital spaces.

■ Rinse and repeat scrub. ■ Dry with a clean towel.

Patient Preoperative Skin Preparation:

■ Clean the area.

■ Apply product to the operative site prior to surgery.

■ 1 mL (dime size) covers an estimated 5”x5” area.

■ Let dry 1-2 minutes.

Healthcare Personnel Handwash Without Water:

■ Place a smaller amount (3 mLs) of product in onehand.

■ Spread over both hands to wrist and rub into

the skin until dry (approximately 30 seconds).

Healthcare Personnel Handwash With Water:

■ Wet clean hands and wrists.

■ Apply 3 milliliters into one hand and spread over both hands to wrist.

■ Rub thoroughly for 30 seconds.

■ Let dry for 30 seconds.

■ Rinse for 30 seconds.

■ Dry with a clean towel.

Other Information

Store in a cool dry place, between 20°-25° C (66°-77° F)

Avoid freezing and excessive heat above 40° C (104° F)

Inactive Ingredients

Allantoin, Beeswax, Benzalkonium Chloride, Butylene, Glycol, C13-14 Isoparaffin, Caprylic/Capric, Triglyceride, Cetyl Alcohol, Disodium EDTA, Distearyl, Dimonium Chloride, Emulsifying Wax, NF, Glyceryl, Laurate, Glyceryl Stearate, Hydrogenated Jojoba Esters, Laureth-7, Nonoxynol-9, Octoxynol-9, PCA, PEG-100 Stearate, Polyacrylamide, Polyglyceryl-3 Diisostearate, Polyquaternium-7, Purified Water, Sclerotium Gum, Stearic Acid, Triethanolamine.

Questions?

Call (877) 710-6958 www.microdermis.com